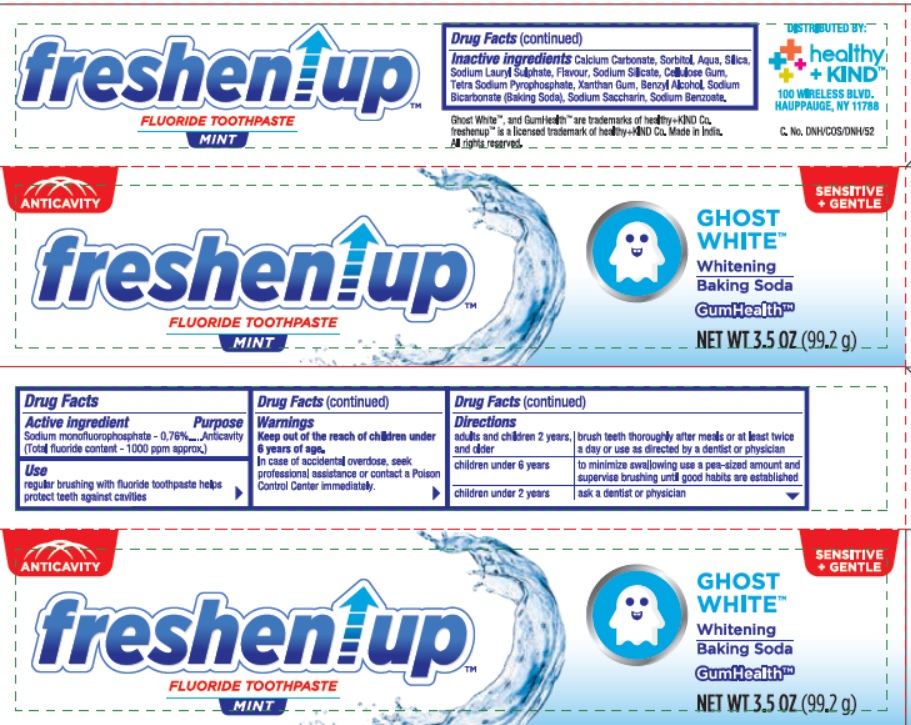 DRUG LABEL: Freshenup Fluoride Mint
NDC: 52553-051 | Form: PASTE, DENTIFRICE
Manufacturer: U. S. Nonwovens Corp
Category: otc | Type: HUMAN OTC DRUG LABEL
Date: 20190814

ACTIVE INGREDIENTS: Sodium Monofluorophosphate 7.6 mg/1 g
INACTIVE INGREDIENTS: CALCIUM CARBONATE; SORBITOL; WATER; SILICON DIOXIDE; SODIUM LAURYL SULFATE; SODIUM SILICATE; SODIUM PYROPHOSPHATE; CARBOXYMETHYLCELLULOSE SODIUM, UNSPECIFIED FORM; XANTHAN GUM; BENZYL ALCOHOL; SODIUM BICARBONATE; SODIUM BENZOATE; SACCHARIN SODIUM

Freshenup Fluoride Toothpaste

Drug Facts

Active ingredient

Sodium monofluorophosphate 0.76% (Total Fluoride Content - 1000 ppm approx)

Purpose

Anticavity

Use

regular brushing with fluoride toothpaste helps protect teeth against cavities

Warnings

Keep out of the reach of children under 6 years of age. In case of accidental overdose, seek professional assistance or contact a Poison Control Center right away.

Directions

adults and children 2 years and older | brush teeth thoroughly after meals or at least twice a day or use as directed by a dentist or physician
children under 6 years | to minimize swallowing use a pea sized amount and supervise brushing until good habits are established
children under 2 years | ask a dentist or physician

Inactive ingredients

Calcium Carbonate, Sorbitol, Aqua, Silica, Sodium Lauryl Sulphate, Flavour, Sodium Silicate, Tetra Sodium Pyrophosphate, Cellulose Gum, Xanthan Gum, Benzyl Alcohol, Sodium Bicarbonate (Baking Soda), Sodium Saccharin, Sodium Benzoate.

Ghost WhiteTM and GumHealthTM are trademarks of healthy+KIND Co.

freshenupTM is a licensed trademark of health+KIND Co. Made In India. All rights reserved

PRINCIPAL DISPLAY PANEL

NDC 52553-051-02

ANTICAVITY

Freshenup

FLUORIDE TOOTHPASTE

MINT

SENSITIVE + GENTLE

GHOST WHITETM

Whitening Baking Soda

GumHealthTM

NET WT 3.5 OZ (99.2 g)